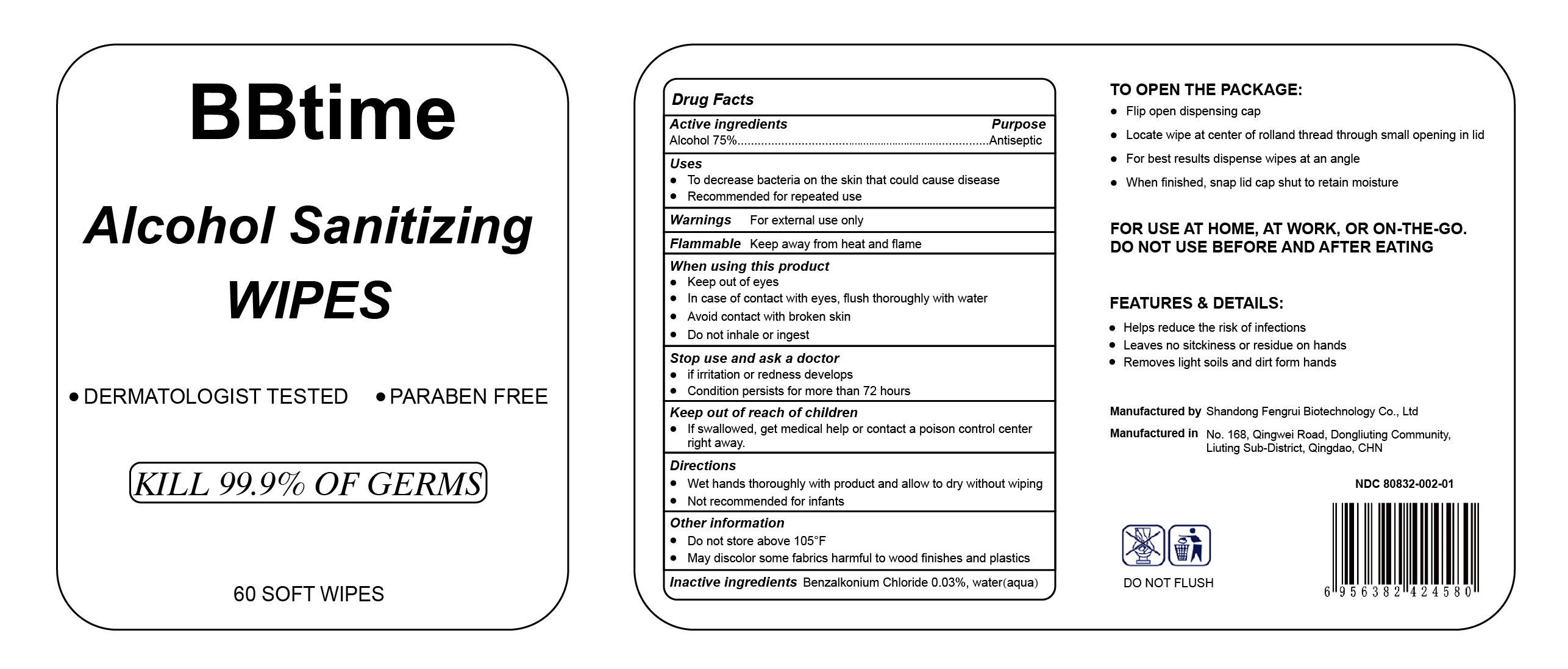 DRUG LABEL: BBtime Alcohol Sanitizing Wipes
NDC: 80832-002 | Form: CLOTH
Manufacturer: Qingdao Fengrui Biotechnology Co., Ltd.
Category: otc | Type: HUMAN OTC DRUG LABEL
Date: 20201019

ACTIVE INGREDIENTS: ALCOHOL 75 mL/100 mL
INACTIVE INGREDIENTS: WATER; BENZALKONIUM CHLORIDE

ACTIVE INGREDIENT

alcohol 75%

PURPOSE

antiseptic

Uses:

- to decrease bacteria on the skin that could cause disease
- Recommended for repeated use

Warnings: For external use only

Flammable: keep away form heat and flame

WHEN USING

- Keep out of eyes
- In case of contact with eyes, flush thoroughly with water
- Avoid contact with broken skin
- Do not inhale or ingest

Stop use and ask a doctor

- if irritation ro redness develops
- condition persists for more than 72 hours

KEEP OUT OF REACH OF CHILDREN

If swallowed, get medical help or contact a poison control center right away

Directions

- Wet hands thoroughly with prodcut and allow to dry without wiping
- Not recommended for infants

Other information

- Do not store above 105℉
- May discolor some fabrics harmful to wood finished and plastics

INACTIVE INGREDIENT

Benzalkonium Chloride 0.03%, water(aqua)

DERMATOLOGIST TESTED

PARABEN FREE

KILL 99.9% OF GERMS

ALCOHOL FREE

60 SOFT WIPES

TO OPEN PACKAGE

Flip open dispensing cap
Locate wipe at center of rolland thread through small opening in lid
For best results dispense wipes at angle
When finished, snap lid acap shut to retain moisture

For use at home, at work, ro on-the-go.

DO NOT USE BEFORE AND AFTER EATING

Feature & details:

- Helps reduce the risk of infections
- Leaves no stickiness or residue on hands
- Removes light soils and dirt from hands

Manufactured by Shandong Fengrui Biotechnology Co., Ltd.

Manufactured in No.168, Qingwei Road, Dongliuting Community, Liuting sub-district, Qingdao, CHN

DO NOT FLUSH

NDC 80832-002-01

PACKAGE LABEL

60 NDC 80830-002-01